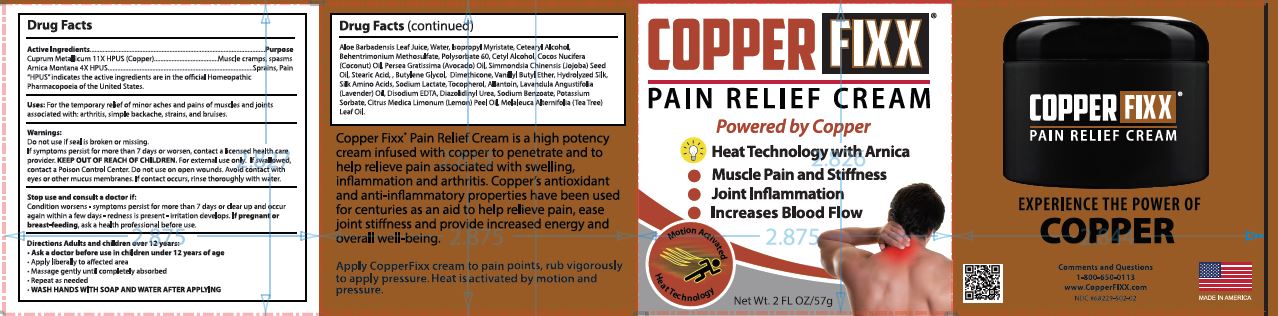 DRUG LABEL: CopperFixx
NDC: 68229-502 | Form: OINTMENT
Manufacturer: Quest Products, Inc.
Category: homeopathic | Type: HUMAN OTC DRUG LABEL
Date: 20241105

ACTIVE INGREDIENTS: COPPER 11 [hp_X]/57 g; ARNICA MONTANA 4 [hp_X]/57 g
INACTIVE INGREDIENTS: ALOE VERA LEAF; WATER; ISOPROPYL MYRISTATE; CETOSTEARYL ALCOHOL; BEHENTRIMONIUM METHOSULFATE; POLYSORBATE 60; CETYL ALCOHOL; COCONUT OIL; AVOCADO OIL; JOJOBA OIL; STEARIC ACID; BUTYLENE GLYCOL; DIMETHICONE; VANILLYL BUTYL ETHER; SILK, ACID HYDROLYZED (1000 MW); AMINO ACIDS, SILK; SODIUM LACTATE; TOCOPHEROL; ALLANTOIN; LAVENDER OIL; EDETATE DISODIUM; DIAZOLIDINYL UREA; SODIUM BENZOATE; POTASSIUM SORBATE; LEMON OIL; TEA TREE OIL

CopperFixx™

Drug Facts

ACTIVE INGREDIENT

Active Ingredients | Purpose
Cuprum Metallicum 11X HPUS | Muscle cramps, spasms
Arnica Montana 4X HPUS | Sprains, Pain
"HPUS" indicates the active ingredients are in the official Homeopathic Pharmacopoeia of the United States.

Uses

For the temporary relief of minor aches and pains of muscles and joints associated with: arthritis, simple backache, strains, and bruises.

Warnings

Do not use if seal is broken or missing.

If symptoms persist for more than 7 days or worsen, contact a licensed health care provider.

KEEP OUT OF REACH OF CHILDREN. For external use only. If swallowed, contact a Poison Control Center. Do not use on open wounds. Avoid contact with eyes or other mucus membranes. If contact occurs, rinse thoroughly with water.

Stop use and consult a doctor if

Condition worsens- symptoms persist for more than 7 days or clear up and occur again within a few days- redness is present- irritation develops. If pregnant or breast- feeding, ask a health professional before use.

Directions

Adults and children over 12 years:

- Ask a doctor before use in children under 12 years of age.
- Apply liberally to affected area.
- Massage gently until completely absorbed.
- Repeat as needed
- WASH HANDS WITH SOAP AND WATER AFTER APPLYING

INACTIVE INGREDIENT

Aloe Barbadensis Leaf Juice, Water, Isopropyl Myristate, Cetearyl Alcohol, Behentrimonium Methosulfate, Polysorbate 60, Cetyl Alcohol, Cocos Nucifera (Coconut) Oil, Persea Gratissima (Avocado) Oil, Simmondsia Chinensis (Jojoba) Seed Oil, Stearic Acid, , Butylene Glycol, Dimethicone, Vanillyl Butyl Ether, Hydrolyzed Silk, Silk Amino Acids, Sodium Lactate, Tocopherol, Allantoin, Lavandula Angustifolia (Lavender) Oil, Disodium EDTA, Diazolidinyl Urea, Sodium Benzoate, Potassium Sorbate, Citrus Medica Limonum (Lemon) Peel Oil, Melaleuca Alternifolia (Tea Tree) Leaf Oil.

PRINCIPAL DISPLAY PANEL - 57 g Jar Carton

COPPER FIXX®

PAIN RELIEF CREAM
Powered by Copper

Heat Technology with Arnica

- Muscle Pain and Stiffness
- Joint Inflammation
- Increases Blood Flow

Net Wt. 2 FL OZ/57g